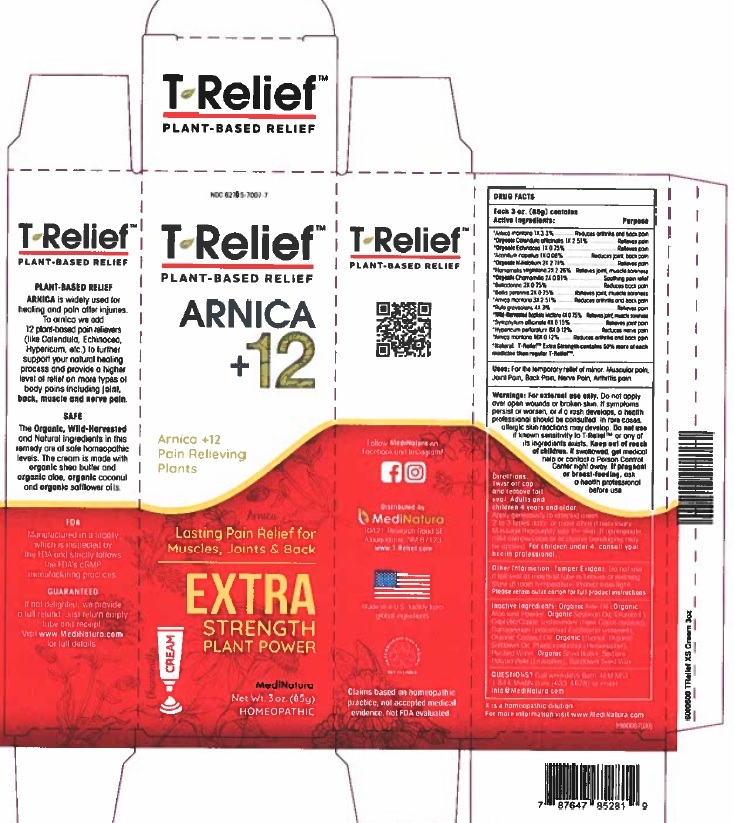 DRUG LABEL: T-Relief Extra Strength Cream
NDC: 62795-7007 | Form: CREAM
Manufacturer: MediNatura Inc
Category: homeopathic | Type: HUMAN OTC DRUG LABEL
Date: 20230927

ACTIVE INGREDIENTS: ARNICA MONTANA 1 [hp_X]/1 g; CALENDULA OFFICINALIS FLOWERING TOP 1 [hp_X]/1 g; ECHINACEA, UNSPECIFIED 1 [hp_X]/1 g; ACONITUM NAPELLUS 1 [hp_X]/1 g; ACHILLEA MILLEFOLIUM 2 [hp_X]/1 g; HAMAMELIS VIRGINIANA ROOT BARK/STEM BARK 2 [hp_X]/1 g; MATRICARIA CHAMOMILLA 2 [hp_X]/1 g; ATROPA BELLADONNA 2 [hp_X]/1 g; BELLIS PERENNIS 2 [hp_X]/1 g; RUTA GRAVEOLENS FLOWERING TOP 4 [hp_X]/1 g; BAPTISIA TINCTORIA ROOT 4 [hp_X]/1 g; COMFREY ROOT 4 [hp_X]/1 g; HYPERICUM PERFORATUM 6 [hp_X]/1 g
INACTIVE INGREDIENTS: WATER; SHEA BUTTER; SODIUM POLYACRYLATE (2500000 MW); HELIANTHUS ANNUUS SEED WAX; ALOE; MEDIUM-CHAIN TRIGLYCERIDES; ALCOHOL; SAFFLOWER OIL; PHENOXYETHANOL; CARRAGEENAN; COCONUT OIL

T-Relief Extra Strength Cream

INGREDIENTS

Arnica montana 1X 3.3%, Calendula officinalis 1X 2.51%, Echinacea 1X 0.75%, Aconitum napellus 1X 0.08%, Millefolium 2X 2.71%, Hamamelis virginiana 2X 2.26%, Chamomilla 2X 0.91%, Belladonna 2X 0.75%, Bellis perennis 2X 0.75%, Arnica montana 3X 2.51%, Ruta graveolens 4X 3%, Baptisia tinctoria 4X 0.75%, Symphytum officinale 4X 0.15%, Hypericum perforatum 6X 0.12%, Arnica montana 10X 0.12%, Natural Ingredients.

INDICATIONS

Pain Relief

KEEP OUT OF REACH OF CHILDREN

USES

For the temporary relief of minor:
• Joint Pain
• Back Pain
• Muscular Pain
• Nerve Pain
• Arthritis Pain

WARNINGS

For external use only. Do not apply over open wounds or broken skin. If symptoms persist or worsen, or if a rash develops, a health professional should be consulted. In rare cases allergic skin reaction may develop. Do not use if known sensitivity to T-Relief or any of its ingredients exists. Keep out of reach of children. If swallowed get medical help or contact a Poison Control Center right away. If pregnant or breast feeding, ask health professional before use.

DIRECTIONS

Twist off cap and remove foil seal. Adults and children 4 and older: Apply generously to affected area 2 to 3 times daily or more often if necessary, as directed by your health professional. Massage thoroughly into the skin. If appropriate, mild compression or occlusive bandaging may be applied. For children under 4, consult your health professional.

INACTIVE INGREDIENT

Organic Aloe Oil, (Organic Aloe Vera Powder, Organic Soybean Oil, Vitamin E) Caprylic/Capric Triglycerides (from Cocos nucifera), Carrageenan (processed Eucheuma seaweed) Organic Coconut Oil, Organic Ethanol, Organic Safflower Oil, Phenoxyethanol,(Preservative), Purified Water, Organic Shea Butter, Sodium Polyacrylate (Emulsifier), Sunflower Seed Wax.